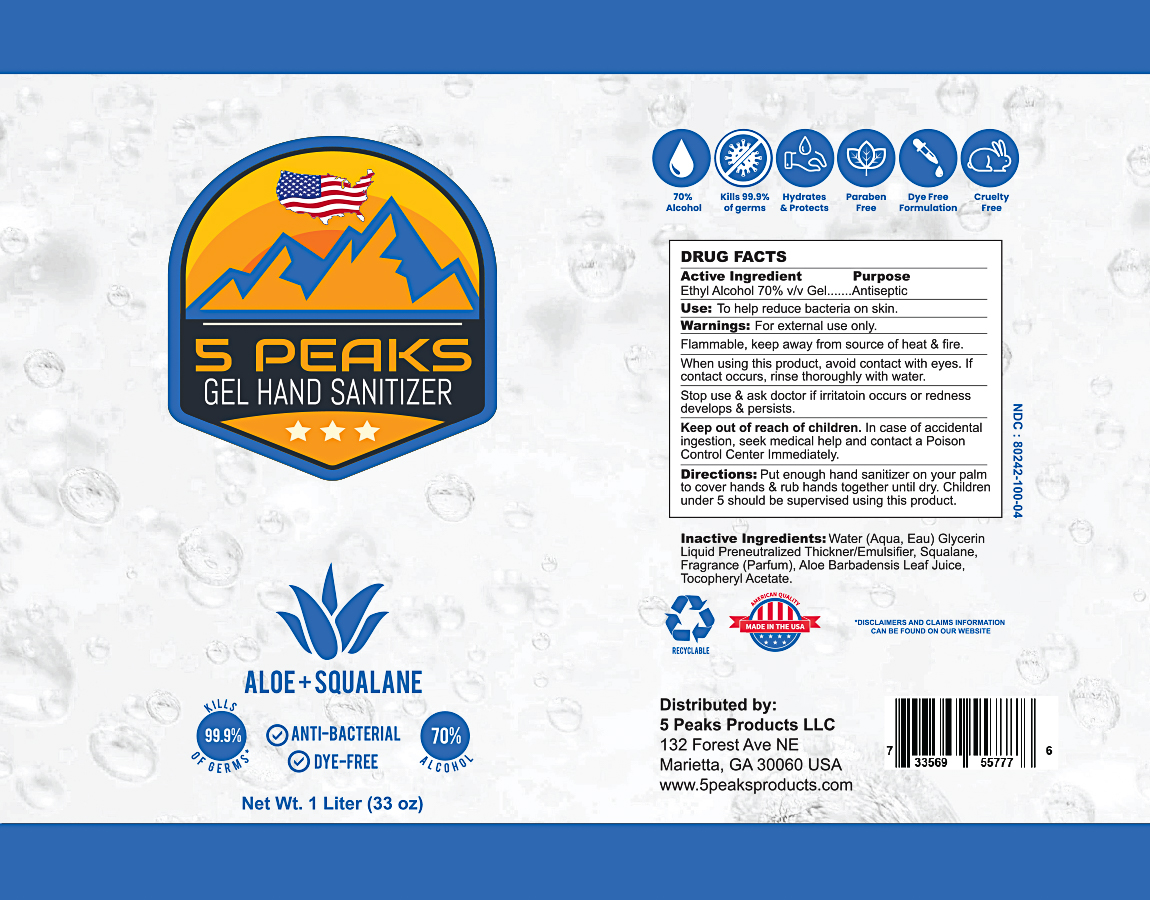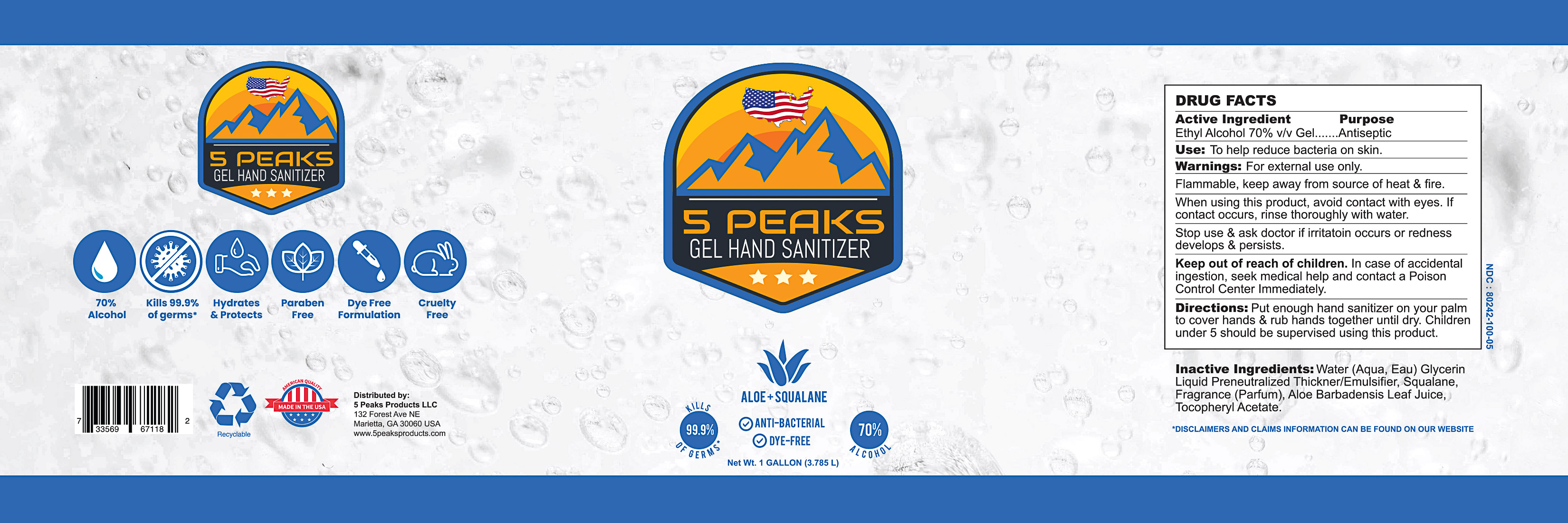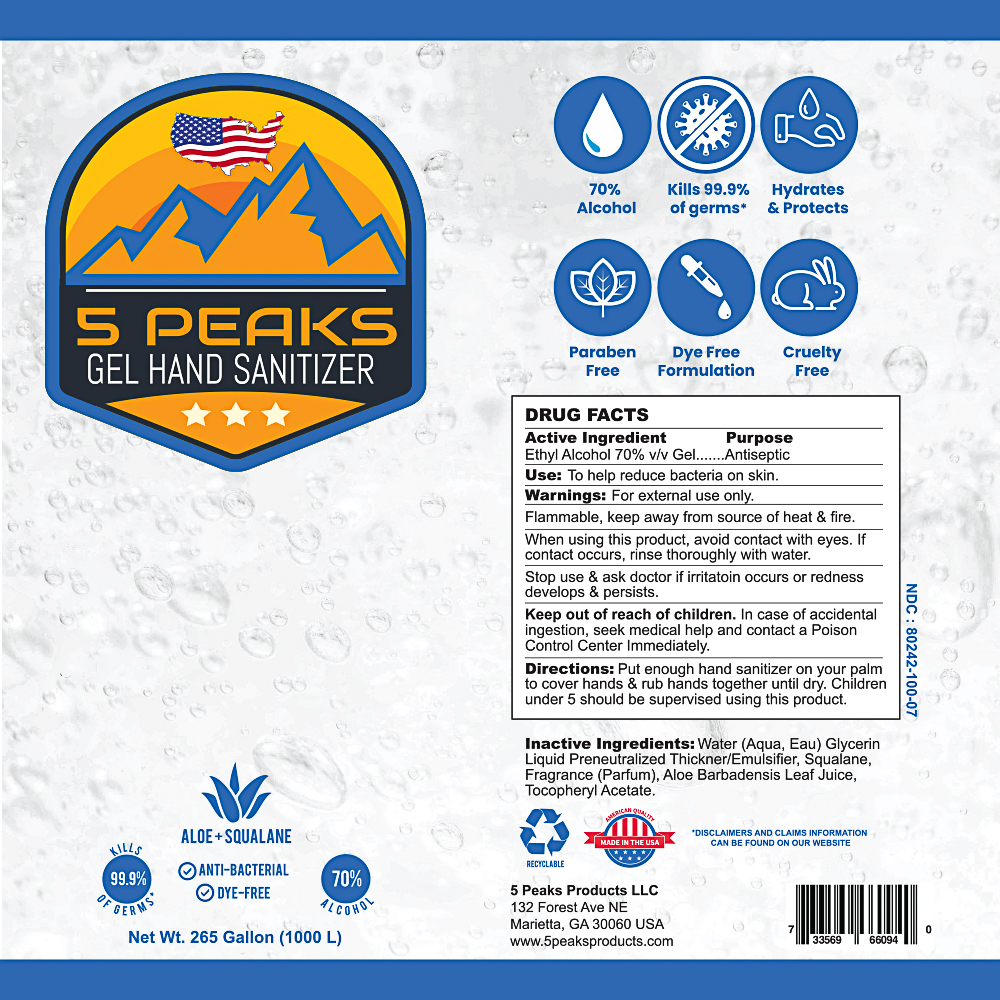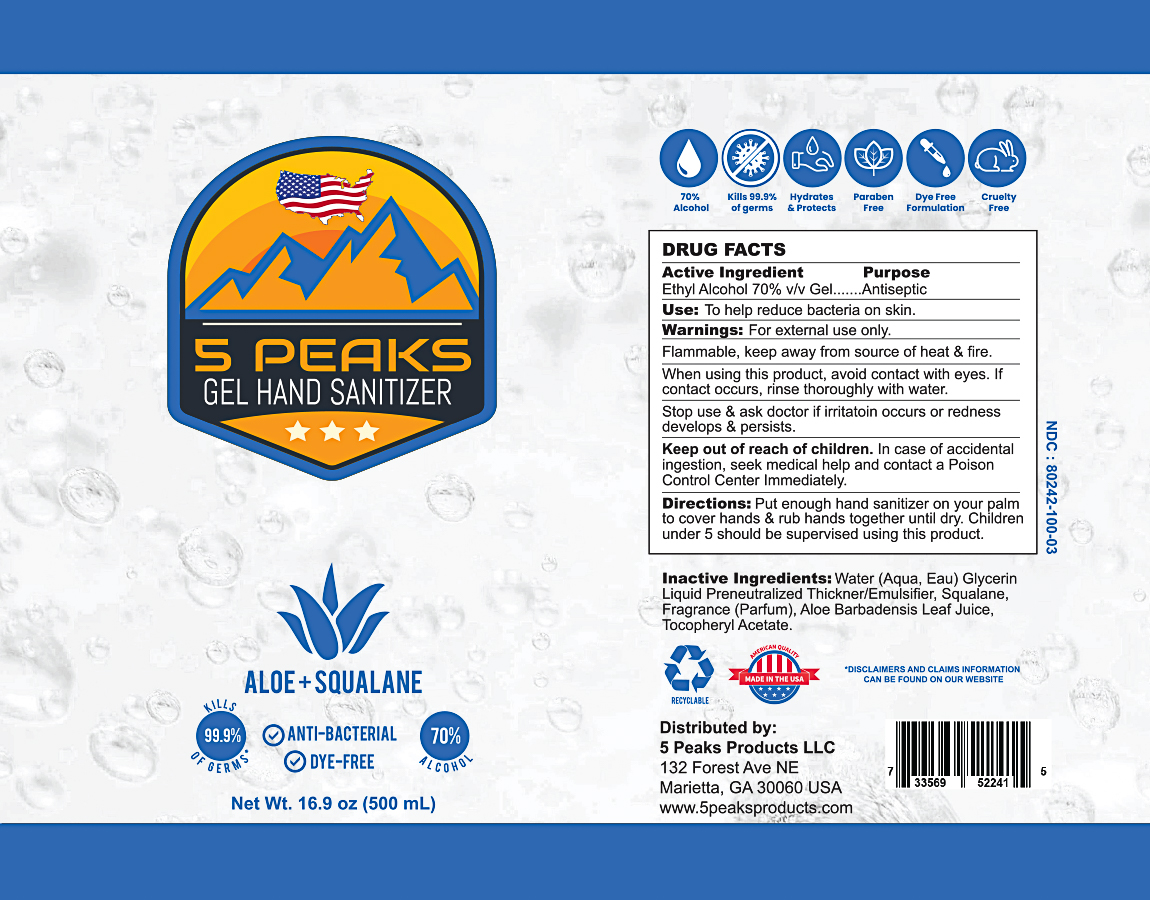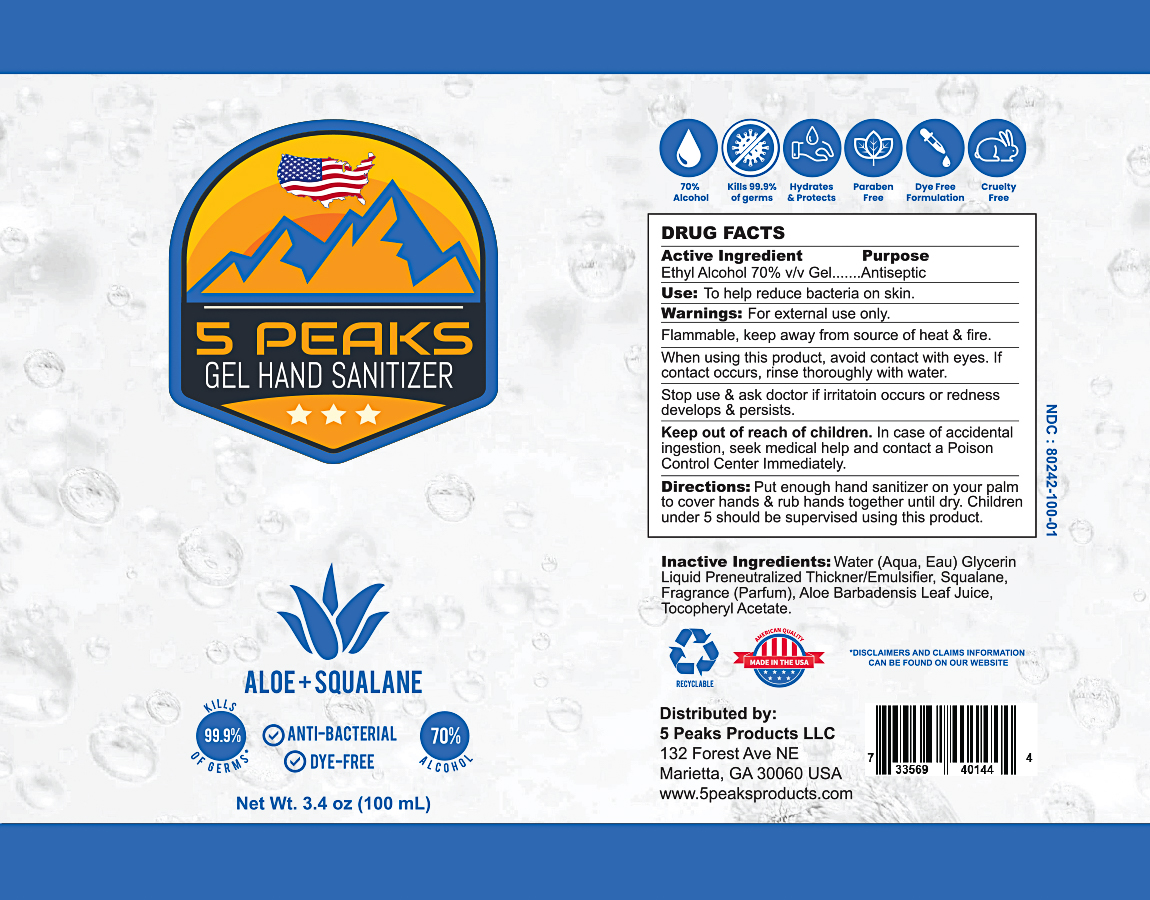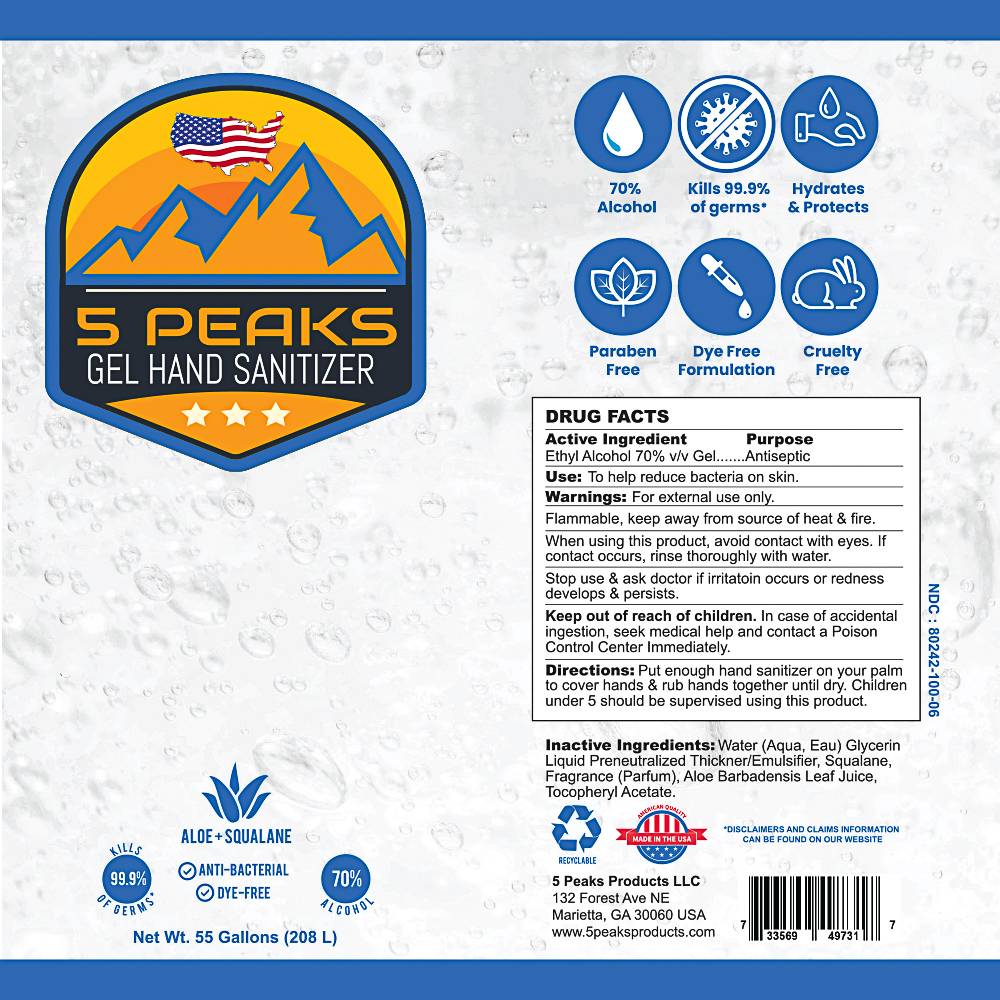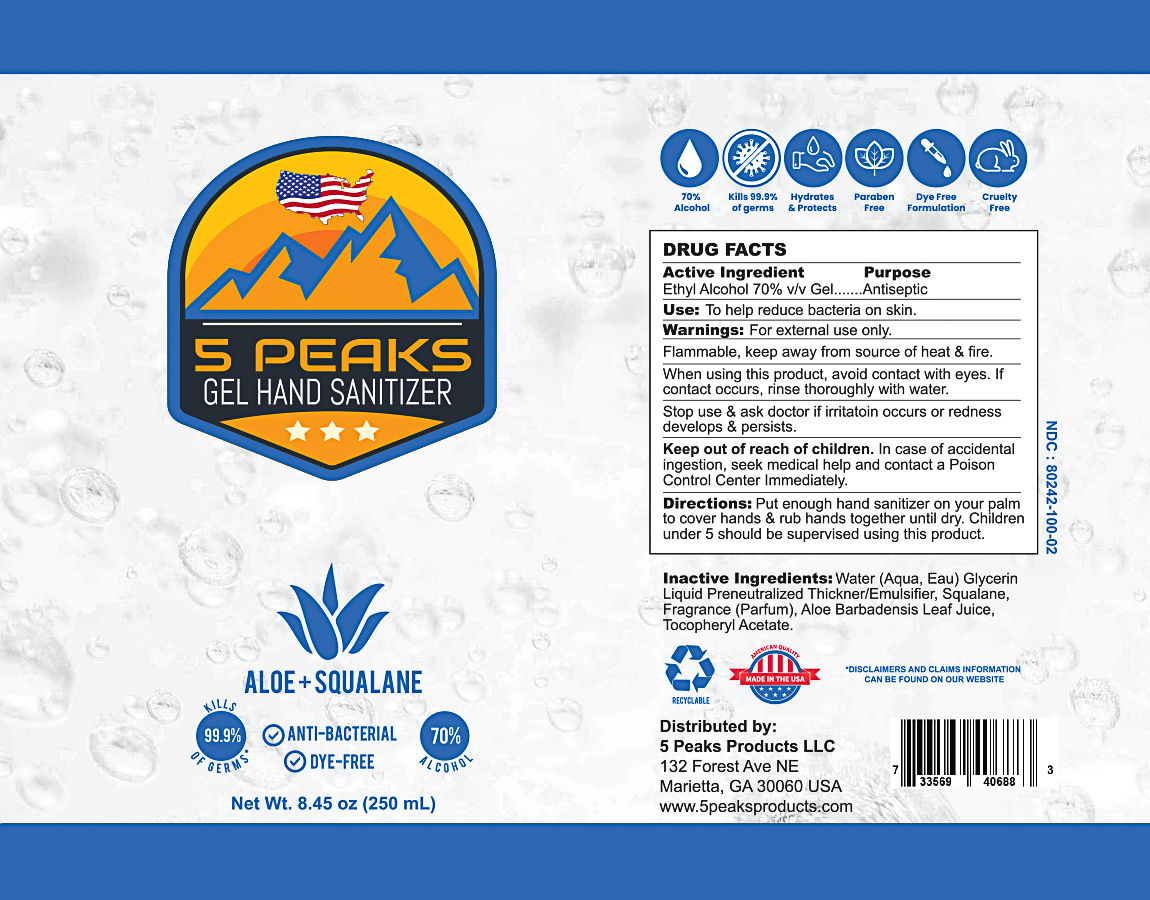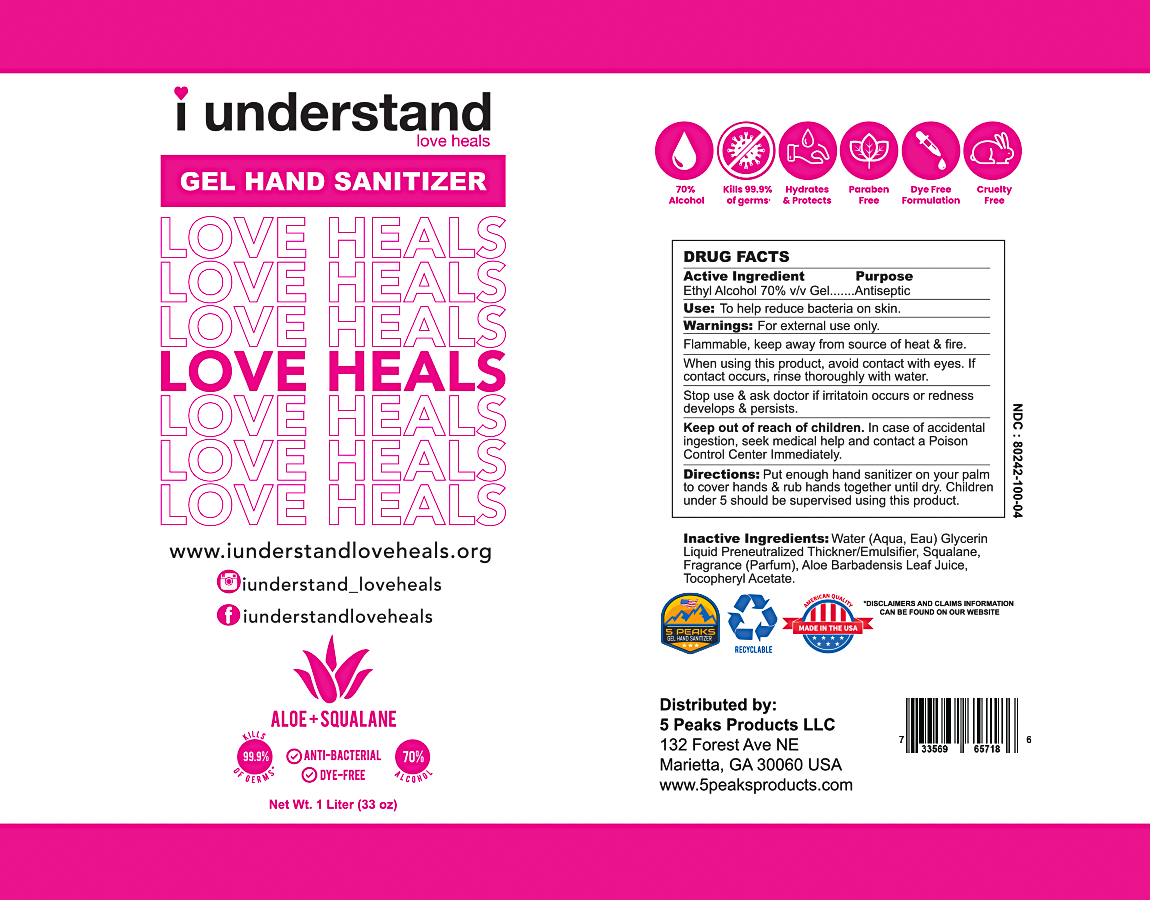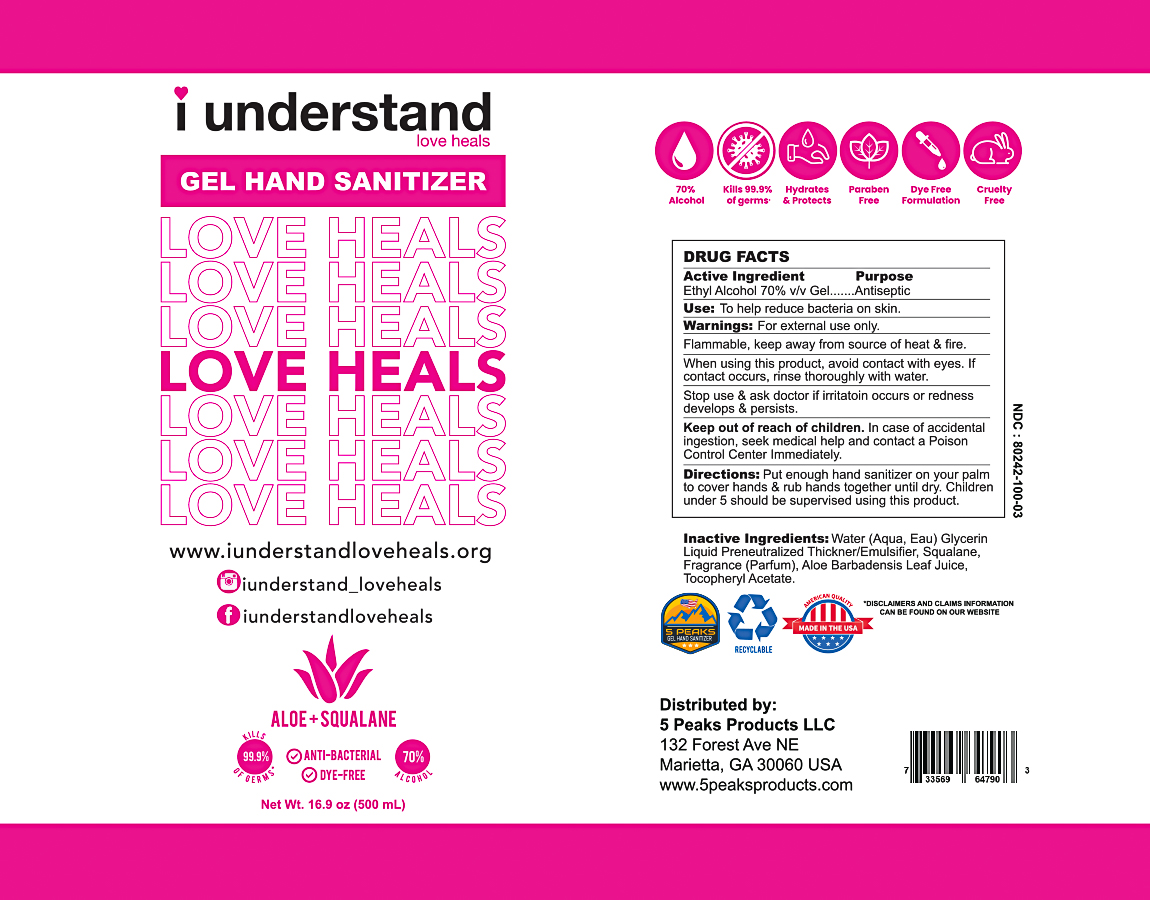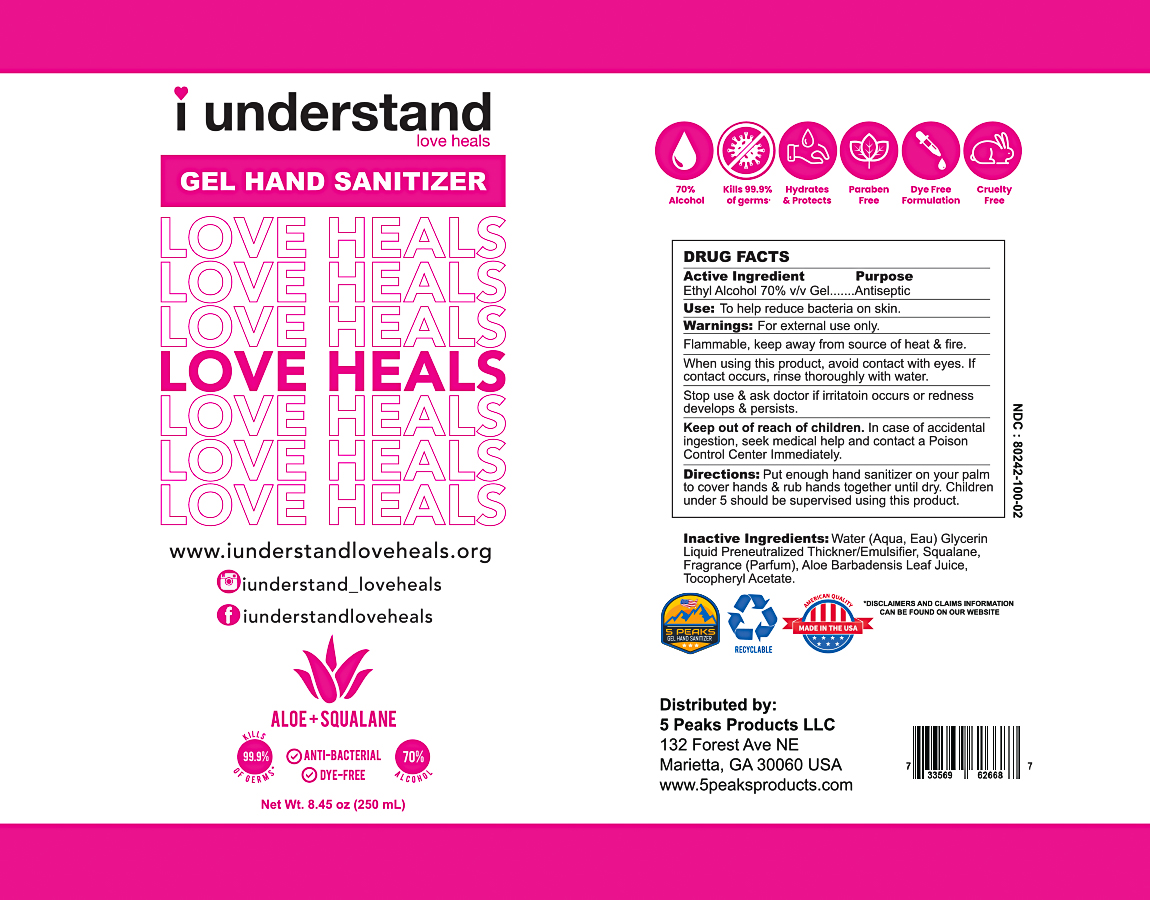 DRUG LABEL: Gel Hand Sanitizer
NDC: 80242-100 | Form: GEL
Manufacturer: 5 Peaks Products, LLC
Category: otc | Type: HUMAN OTC DRUG LABEL
Date: 20200912

ACTIVE INGREDIENTS: ALCOHOL 70 mL/100 mL
INACTIVE INGREDIENTS: .ALPHA.-TOCOPHEROL ACETATE, D-; SQUALANE; RAPIDGEL EZ1; ALOE VERA LEAF; GLYCERIN 1.45 mL/100 mL; WATER

70% Gel Hand Sanitizer

Active Ingredient(s)

Ethyl Alcohol 70% v/v. Purpose: Antiseptic

Purpose

Antiseptic, Hand Sanitizer

Use

To help reduce bacteria on skin.

Warnings

For external use only. Flammable, keep away from source of heat & fire.

When using this product, avoid contact with eyes. If contact occurs, rinse thoroughly with water.

Stop use & ask doctor if irritation occurs or redness develops & persists.

Keep out of reach of children. In case of accidental ingestion, seek medical help and contact a Poison Control Center Immediately.

Directions

Put enough hand sanitizer on your palm to cover hands & rub hands together until dry. Children under 5 should be supervised using this product.

Inactive ingredients

Water (Aqua, Eau), Glycerin, Liquid Preneutralized Thickener/Emulsifier, Squalane, Fragrance (Parfum), Aloe Barbadensis Leaf Juice, Tocopheryl Acetate.

RECENT MAJOR CHANGES

Section 3:
To help reduce bacteria on skin. (09/2020)

Section 8:
Put enough hand sanitizer on your palm to cover hands & rub hands together until dry. Children under 5 should be supervised using this product. (09/2020)

Package Label - Principal Display Panel

100 mL NDC: 80242-100-01

250 mL NDC: 80242-100-02

500 mL NDC: 80242-100-03

1 L NDC: 80242-100-04

3.785 L NDC: 80242-100-05

208 L NDC: 80242-100-06

1000 L NDC: 80242-100-07

iUnderstand Product Label

250 mL NDC: 80242-100-02

500 mL NDC: 80242-100-03

1 L NDC: 80242-100-04